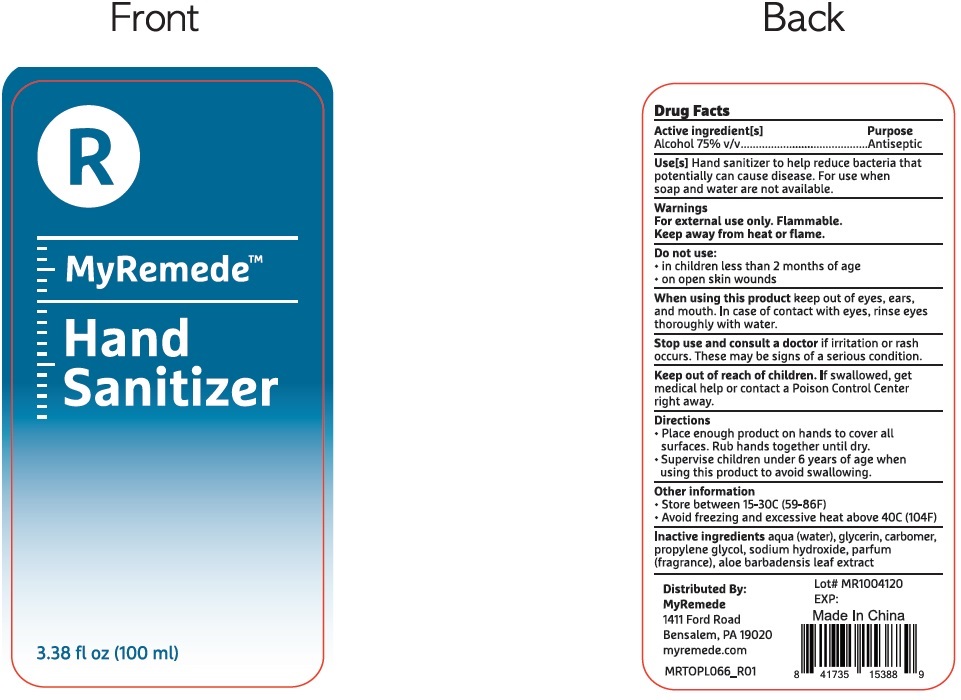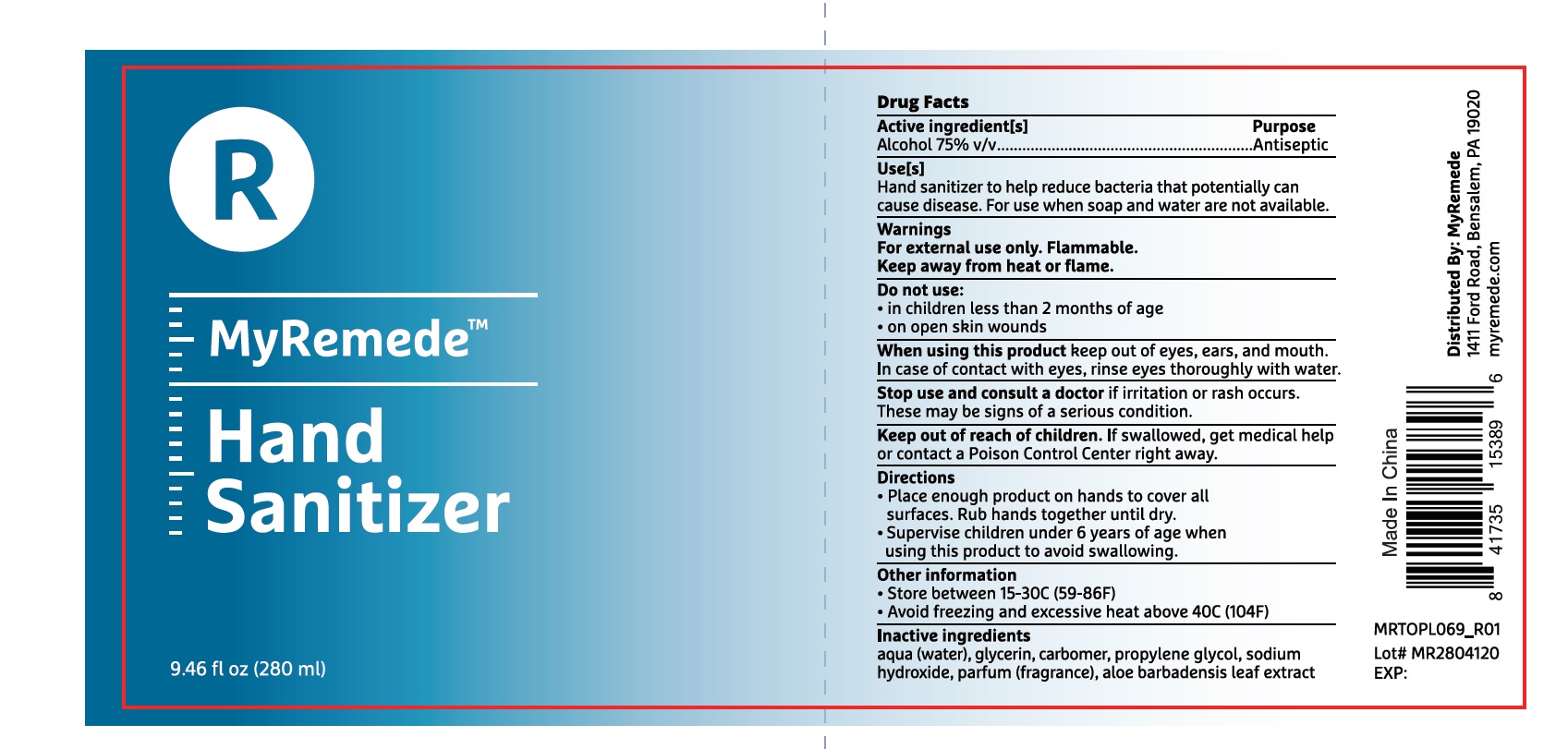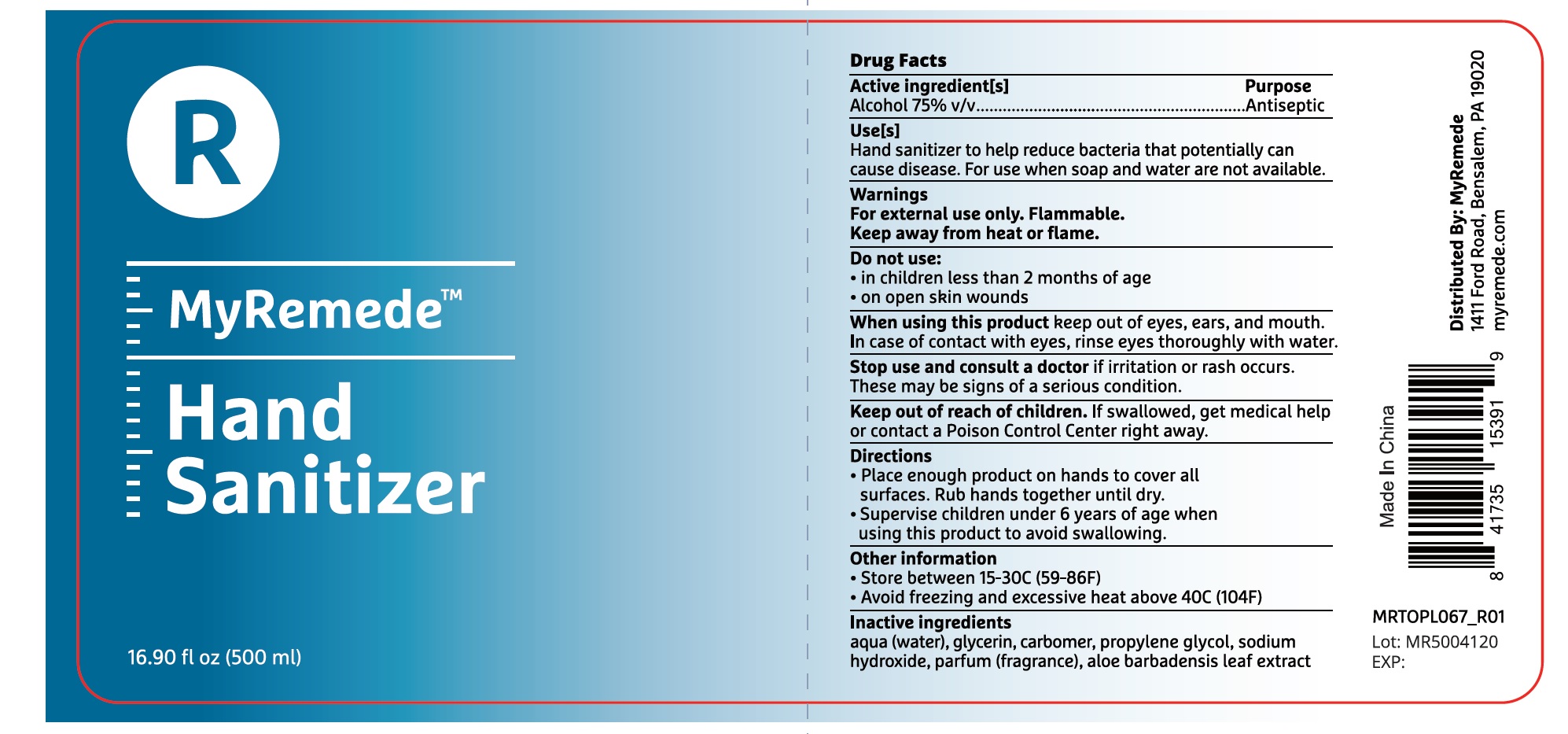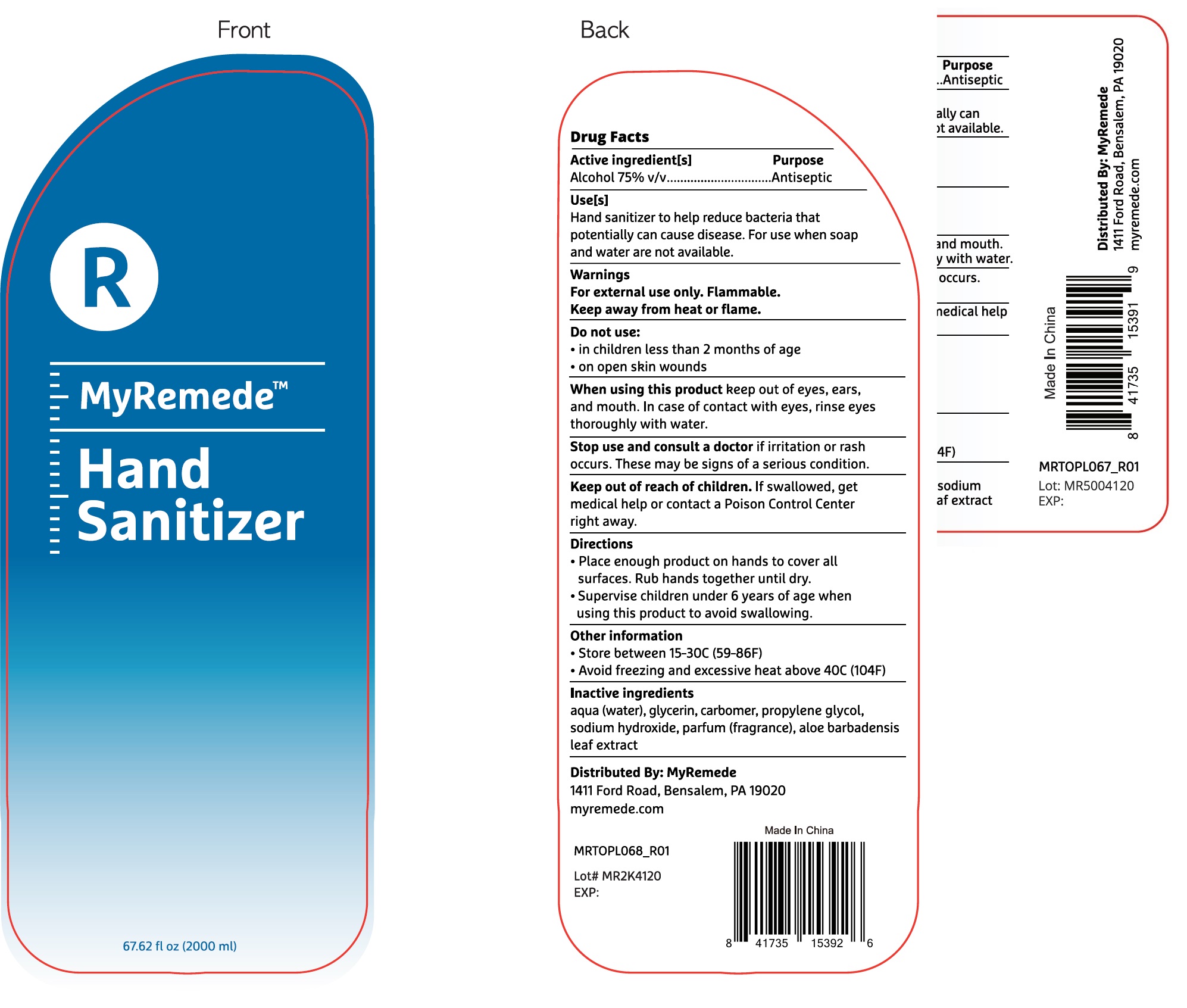 DRUG LABEL: MyRemede Hand Sanitizer
NDC: 77529-000 | Form: GEL
Manufacturer: Remede Organics, Inc.
Category: otc | Type: HUMAN OTC DRUG LABEL
Date: 20200511

ACTIVE INGREDIENTS: ALCOHOL 0.75 mL/1 mL
INACTIVE INGREDIENTS: WATER; GLYCERIN; CARBOMER HOMOPOLYMER, UNSPECIFIED TYPE; PROPYLENE GLYCOL; SODIUM HYDROXIDE; ALOE VERA LEAF

MyRemede Hand Sanitizer

Active ingredients[s]

Alcohol 75% v/v

Purpose

Antiseptic

Uses[s]

Hand sanitizer to help reduse bacteria that potentially can cause disease. For use when stop and water are not available.

warnings

For external use only. Flammable.

Keep away from heat or flame.

Do not use:

- in children less than 2 months of age
- on open skin wounds

When using this product

keep out of eyes, ears and mouth. In case of contact with eyes, rinse eyes thoroughly with water.

Stop use and consult a doctor

if irritation or rash occurs. These may be signs of a serious condition.

Keep out of reach of children.

If swallowed, get medical help or contact a Poison Control Center right away.

Directions

- Place enough product on hands to cover all surfaces. Rub hands together until dyr.
- Supervise children under 6 years of age when using this product to avoid swallowing.

Other information

- Store between 15-30C (59-86F)
- Avoid freezing and excessive heat above 40C (104F)

Inactive ingredients

aqua (water), glycerin, carbomer, propylene glycol, sodium hydroxide, parfum (fragrance), aloe barbadensis leaf extract

Package Labeling 280ml

Lable2